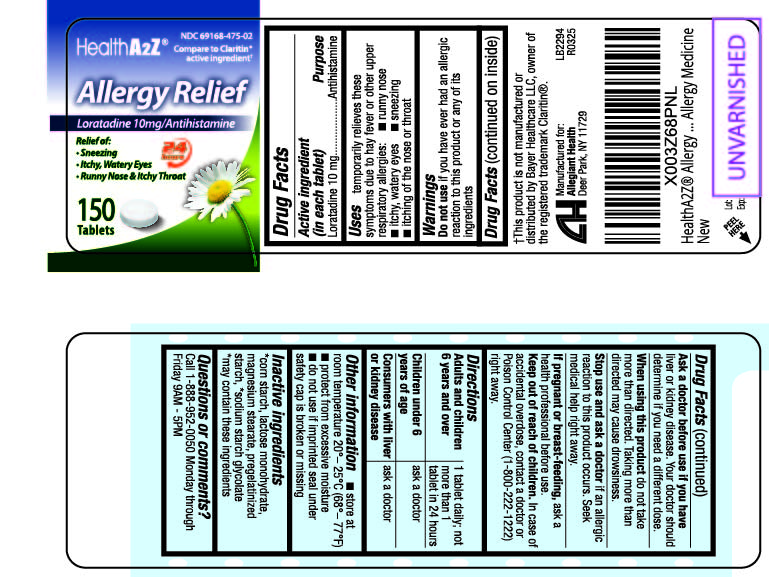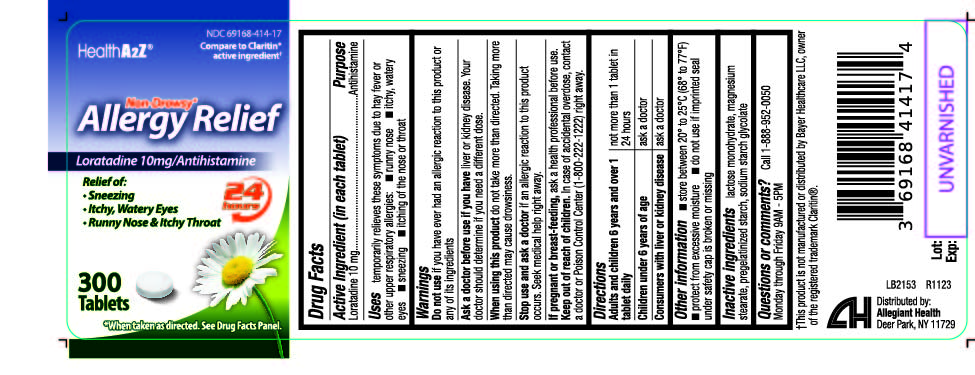 DRUG LABEL: Allergy Relief
NDC: 69168-414 | Form: TABLET
Manufacturer: Allegiant Health
Category: otc | Type: HUMAN OTC DRUG LABEL
Date: 20200616

ACTIVE INGREDIENTS: LORATADINE 10 mg/1 1
INACTIVE INGREDIENTS: LACTOSE MONOHYDRATE; MAGNESIUM STEARATE

309 - Health A2Z Allergy Relief

Active ingredient (in each tablet)

Loratadine 10mg

Purpose

Antihistamine

Uses

temporarily relieves these symptoms due to hay fever or other upper respiratory allergies:

- runny nose
- itchy, watery eyes
- sneezing
- itching of the nose or throat

Warnings

Do not use

if you have ever had an allergic reaction to this product or any of its ingredients

Ask a doctor before use if you have

liver or kidney disease. Your doctor should determine if you need a different dose.

When using this product

do not take more than directed. Taking more than directed may cause drowsiness.

Stop use and ask a doctor

if an allergic reaction to this product occurs. Seek medical help right away.

Pregnancy/Breastfeeding

ask a health professional before use.

Keep out of reach of children

In case of accidental overdose, contact a doctor or Poison Control Center (1-800-222-1222) right away.

Directions

Adults and children 6 years and over: 1 tablet daily; not more than 1 tablet in 24 hours

Children under 6 years of age: ask a doctor

Consumers with liver or kidney disease: ask a doctor

Other information

- store between 20° to 25°C (68° to 77°F)
- protect from excessive moisture
- do not use if imprinted seal under safety cap is broken or missing

Inactive ingredients

*corn starch, lactose monohydrate, magnesium stearate ,
pregelantinized starch, *sodium starch glycolate

*May contain these ingredients

Principal Display Panel

Loratadine 10mg
Loratadine 10mg